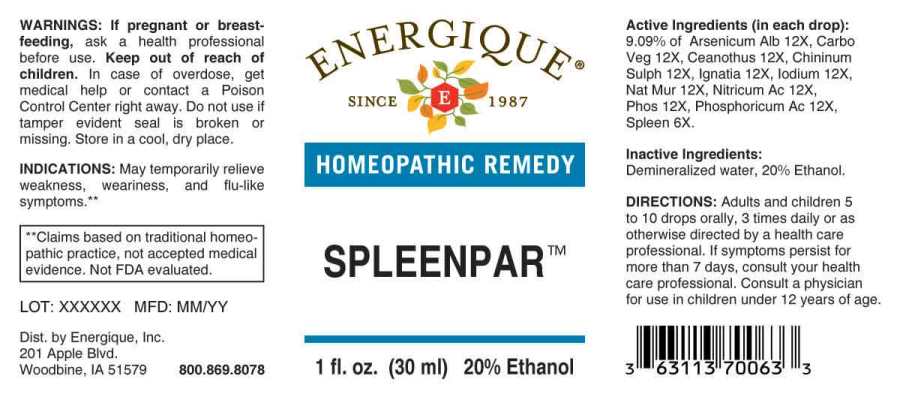 DRUG LABEL: Spleenpar
NDC: 44911-0261 | Form: LIQUID
Manufacturer: Energique, Inc.
Category: homeopathic | Type: HUMAN OTC DRUG LABEL
Date: 20241030

ACTIVE INGREDIENTS: SUS SCROFA SPLEEN 6 [hp_X]/1 mL; ARSENIC TRIOXIDE 12 [hp_X]/1 mL; ACTIVATED CHARCOAL 12 [hp_X]/1 mL; CEANOTHUS AMERICANUS LEAF 12 [hp_X]/1 mL; QUININE SULFATE 12 [hp_X]/1 mL; STRYCHNOS IGNATII SEED 12 [hp_X]/1 mL; IODINE 12 [hp_X]/1 mL; SODIUM CHLORIDE 12 [hp_X]/1 mL; NITRIC ACID 12 [hp_X]/1 mL; PHOSPHORIC ACID 12 [hp_X]/1 mL; PHOSPHORUS 12 [hp_X]/1 mL
INACTIVE INGREDIENTS: WATER; ALCOHOL

DRUG FACTS:

ACTIVE INGREDIENTS:

(in each drop): 9.09% of Arsenicum Album 12X, Carbo Vegetabilis 12X, Ceanothus Americanus 12X, Chininum Sulphuricum 12X, Ignatia Amara 12X, Iodium 12X, Natrum Muriaticum 12X, Nitricum Acidum 12X, Phosphoricum Acidum 12X, Phosphorus 12X, Spleen (Suis) 6X.

INDICATIONS:

May temporarily relieve weakness, weariness, and flu-like symptoms.**

**Claims based on traditional homeopathic practice, not accepted medical evidence. Not FDA evaluated.

WARNINGS:

If pregnant or breast-feeding, ask a health professional before use.

Keep out of reach of children. In case of overdose, get medical help or contact a Poison Control Center right away.

Do not use if tamper evident seal is broken or missing. Store in a cool, dry place.

Keep out of reach of children. In case of overdose, get medical help or contact a Poison Control Center right away.

DIRECTIONS:

Adults and children 5 to 10 drops orally, 3 times daily or as otherwise directed by a health care professional. If symptoms persist for more than 7 days, consult your health care professional.

Consult a physician for use in children under 12 years of age.

INDICATIONS:

May temporarily relieve weakness, weariness, and flu-like symptoms.**

**Claims based on traditional homeopathic practice, not accepted medical evidence. Not FDA evaluated.

INACTIVE INGREDIENTS:

Demineralized water, 20% Ethanol.

QUESTIONS:

Dist. by Energique, Inc.

201 Apple Blvd

Woodbine, IA 51579 800.869.8078

PACKAGE LABEL DISPLAY:

ENERGIQUE

SINCE 1987

HOMEOPATHIC REMEDY

SPLEENPAR

1 fl. oz. (30 ml)